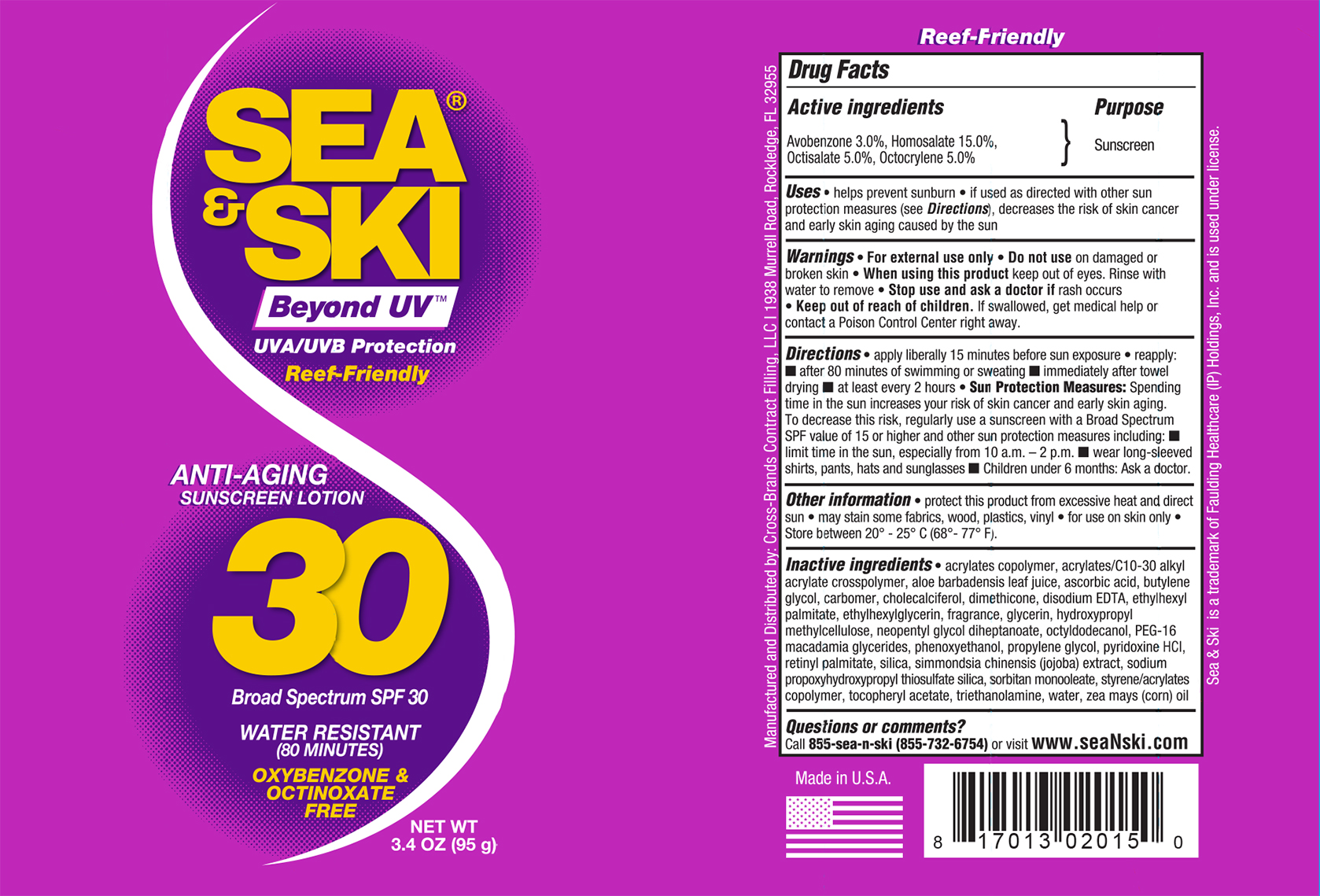 DRUG LABEL: Sea and Ski SPF 30
NDC: 73440-2015 | Form: LOTION
Manufacturer: Cross-Brands Contract Filling
Category: otc | Type: HUMAN OTC DRUG LABEL
Date: 20210219

ACTIVE INGREDIENTS: AVOBENZONE 2.85 g/95 g; HOMOSALATE 14.25 g/95 g; OCTISALATE 4.75 g/95 g; OCTOCRYLENE 4.75 g/95 g
INACTIVE INGREDIENTS: WATER 49.5 g/95 g

Sea&Ski SPF 30 lotion 3.4oz